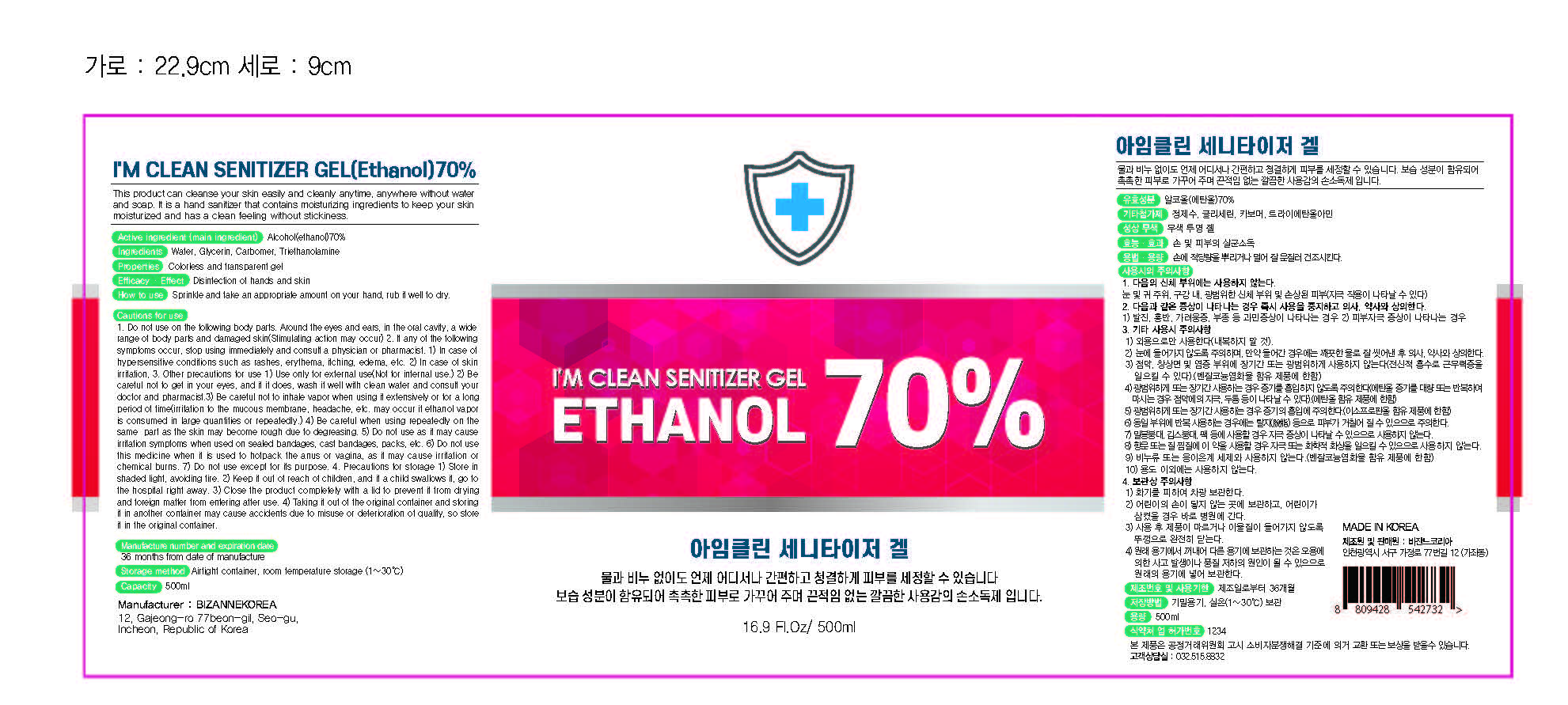 DRUG LABEL: IM CLEAN SANITIZER Gel
NDC: 79274-0001 | Form: GEL
Manufacturer: Bizanne Korea
Category: otc | Type: HUMAN OTC DRUG LABEL
Date: 20200624

ACTIVE INGREDIENTS: ALCOHOL 350 mL/500 mL
INACTIVE INGREDIENTS: WATER; TROLAMINE; CARBOMER HOMOPOLYMER, UNSPECIFIED TYPE; GLYCERIN

Bizanne Korea - IM CLEAN SANITIZER Gel

ACTIVE INGREDIENT

Alcohol

INACTIVE INGREDIENT

water, glycerin, triethanolamine, carbomer

PURPOSE

Antiseptic

keep out of reach of the children

INDICATIONS AND USAGE

Sprinkle and take an appropriate amount on your hand, rub it well to dry.

WARNINGS

1. Do not use on the following body parts. Around the eyes and ears, in the oral cavity, a wide range of body parts and damaged skin(Stimulating action may occur)

2. If any of the following symptoms occur, stop using immediately and consult a physician or pharmacist.

1) In case of hypersensitive conditions such as rashes, erythema, itching, edema, etc.

2) In case of skin irritation,

3. Other precautions for use

1) Use only for external use(Not for internal use.)

2) Be careful not to get in your eyes, and if it does, wash it well with clean water and c onsult your doctor and pharmacist.

3) Be careful not to inhale vapor when using it extensively or for a long period of time(irritation to the muc ous membrane, headache, etc. may occur if ethanol vapor is consumed in large quantities or repeatedly.)

4) Be careful when using repeatedly on the same part as the skin may become rough due to degreasing.

5) Do not use as it may cause irritation symptoms when used on sealed bandages, cast bandages, packs, etc.

6) Do not use this medicine when it is use d to hotpack the anus or v agina, as it ma y cause irritation or chemical burns.

7) Do not use except for its purpose.

4. Precautions for storage

1) Store in shaded light, avoiding fire.

2) Keep it out of reach of children, and if a child swallows it, go to the hospital right away.

3) Close the product completely with a lid to pr event it from drying and foreign matter from entering after use.

4) Taking it out of the original container and storing it in another container may cause accidents due to misuse or deterioration of quality, so store it in the original container.

DOSAGE AND ADMINISTRATION

for external use only